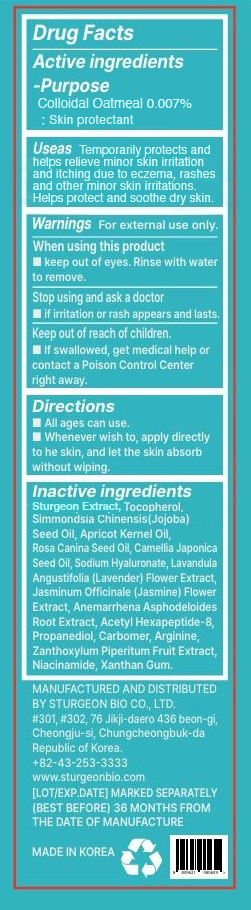 DRUG LABEL: The Zoeun Omega Serum
NDC: 83636-115 | Form: GEL
Manufacturer: Sturgeonbio Co.,Ltd.
Category: otc | Type: HUMAN OTC DRUG LABEL
Date: 20251031

ACTIVE INGREDIENTS: OATMEAL 0.007 g/100 mL
INACTIVE INGREDIENTS: PRUNUS ARMENIACA SEED; ANEMARRHENA ASPHODELOIDES ROOT; NIACINAMIDE; XANTHAN GUM; SODIUM HYALURONATE; CARBOMER HOMOPOLYMER, UNSPECIFIED TYPE; CAMELLIA JAPONICA SEED OIL; ACETYL HEXAPEPTIDE-8; ROSA CANINA SEED OIL; TOCOPHEROL; JASMINUM OFFICINALE (JASMINE) FLOWER; STURGEON, UNSPECIFIED; ZANTHOXYLUM PIPERITUM FRUIT PULP; LAVANDULA ANGUSTIFOLIA (LAVENDER) FLOWER; ARGININE; SIMMONDSIA CHINENSIS (JOJOBA) SEED OIL; PROPANEDIOL

115 THE ZOEUN OMEGA SERUM

Active Ingredients

Colloidal Oatmeal 0.007%

Purpose

Skin protectant.

Uses

Temporarily protects and helps relieve minor skin irritation and itching due to eczema, rashes, insect bites, and other minor skin irritations. Helps protect and soothe dry skin

Warnings

- Keep out of reach of children.
- If swallowed, get medical help or contact a Poison Control Center right away.

Warnings

Stop using and ask a doctor if irritation or rash appears and lasts.

Warnings

When using this product keep out of eyes. Rinse with water to remove.

Warnings

For external use only.

Directions

- All ages can use.
- Whenever wish to, apply directly to the skin, and let the skin absorb without wiping.

Inactive Ingredients

Sturgeon Extract, Tocopherol, Simmondsia Chinensis (Jojoba) Seed Oil, Apricot Kernel Oil, Rosa Canina Seed Oil,
Camellia Japonica Seed Oil, Sodium Hyaluronate, Lavandula Angustifolia (Lavender) Flower Extract,
Jasminum Officinale (Jasmine) Flower Extract, Anemarrhena Asphodeloides Root Extract, Acetyl Hexapeptide-8,
Propanediol, Carbomer, Arginine, Zanthoxylum Piperitum Fruit Extract, Niacinamide, Xanthan Gum.